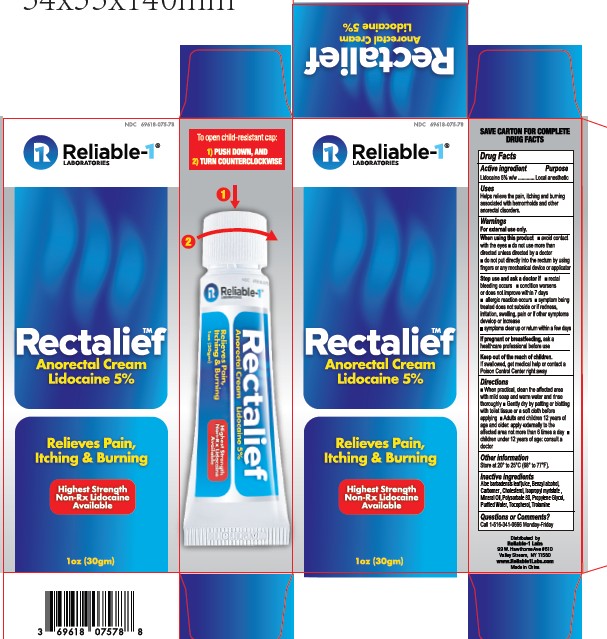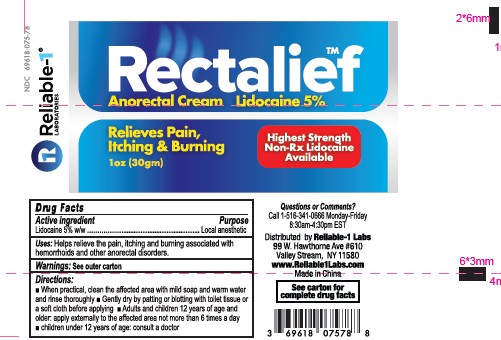 DRUG LABEL: RETALIEF LIDOCAINE 5
NDC: 69618-075 | Form: CREAM
Manufacturer: Reliable 1 Laboratories LLC
Category: otc | Type: HUMAN OTC DRUG LABEL
Date: 20250120

ACTIVE INGREDIENTS: LIDOCAINE 0.05 g/1 g
INACTIVE INGREDIENTS: TOCOPHEROL; BENZYL ALCOHOL; ALOE BARBADENSIS LEAF JUICE; CHOLESTEROL; ISOPROPYL MYRISTATE; MINERAL OIL; PROPYLENE GLYCOL; TROLAMINE; POLYSORBATE 80; WATER; CARBOMER

RECTALIEF LIDOCAINE 5 CREAM

ACTIVE INGREDIENT

Lidocaine 5% W/W

PURPOSE

Local Anesthetic Anorectal (Hemorrhoidal) Cream

INDICATIONS AND USAGE

helps relieve the pain, itching, and burning, associated with hemorrhoids and anorectal disorders

WARNINGS

FOR EXTERNAL USE ONLY

When using this product

- avoid contact with eyes
- do not use more than directed unless directed by a doctor
- do not put directly into the rectum by using fingers or any mechanical device or applicator

Stop use and ask a doctor if

- rectal bleeding occurs
- condition worsens or does not improve within 7 days
- an allergic reaction occurs
- symptom being treated does not subside or if redness, irritation, swelling, pain or other symptoms develop or increase
- symptoms clear up and occur again within a few days

PREGNANCY OR BREAST FEEDING

If pregnant or breast-feeding, ask a health professional before use.

Keep out of reach of children.

If swallowed, get medical help or contact a Poison Control Center right away

DIRECTIONS

- when practical, cleanse the affected area with mild soap and warm water and rinse thoroughly.
- Gently dry by patting or blotting with toilet tissue or a soft cloth before applying
- Adults and children 12 years of age and older: apply externally to the affected area not more than 6 times a day.
- children under 12 years of age: consult a doctor.

OTHER SAFETY INFORMATION

Store between 20°-25° C (68°-77° F)

INACTIVE INGREDIENT

Aloe barbadensis leaf juice, Benzyl alcohol, Carbomer, Cholesterol, Isopropyl myristate, Mineral Oil, Polysorbate 80, Propylene Glycol, Purified Water, Tocopherol, Trolamine.

PACKAGE LABEL

NDC 69618-075-78

Reliable 1 Laboratories

Rectalief

Anorectal Cream

Lidocaine 5%

Relieves Pain, Itching & Burning

Highest Strength of Non-Rx Lidocaine Available

1OZ (30gm)

QUESTIONS

1-516-341-0666 Monday- Friday

Distributed by

Reliable 1 Labs

99 W. Hawthorne Ave #610

Valley Stream, NY 11580

www.reliable1labs.com

Made in China